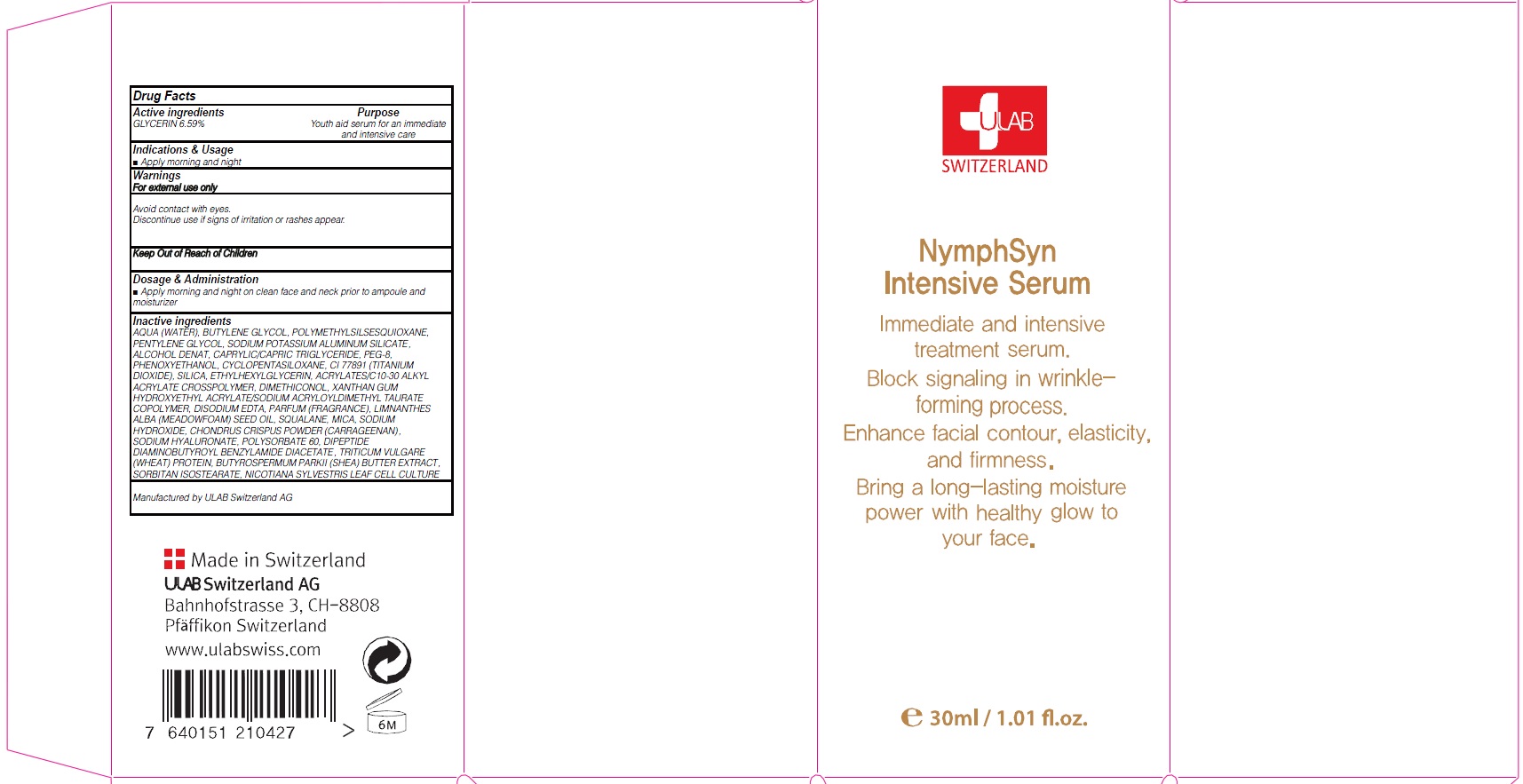 DRUG LABEL: NYMPHSYN INTENSIVE SERUM
NDC: 71276-050 | Form: CREAM
Manufacturer: ULAB
Category: otc | Type: HUMAN OTC DRUG LABEL
Date: 20170321

ACTIVE INGREDIENTS: GLYCERIN 1.97 g/30 mL
INACTIVE INGREDIENTS: WATER; BUTYLENE GLYCOL

ACTIVE INGREDIENT

Active ingredients: GLYCERIN 6.59%

INACTIVE INGREDIENT

Inactive ingredients: AQUA (WATER), BUTYLENE GLYCOL, POLYMETHYLSILSESQUIOXANE, PENTYLENE GLYCOL, SODIUM POTASSIUM ALUMINUM SILICATE, ALCOHOL DENAT, CAPRYLIC/CAPRIC TRIGLYCERIDE, PEG-8, PHENOXYETHANOL, CYCLOPENTASILOXANE, CI 77891 (TITANIUM DIOXIDE), SILICA, ETHYLHEXYLGLYCERIN, ACRYLATES/C10-30 ALKYL ACRYLATE CROSSPOLYMER, DIMETHICONOL, XANTHAN GUM HYDROXYETHYL ACRYLATE/SODIUM ACRYLOYLDIMETHYL TAURATE COPOLYMER, DISODIUM EDTA, PARFUM (FRAGRANCE), LIMNANTHES ALBA (MEADOWFOAM) SEED OIL, SQUALANE, MICA, SODIUM HYDROXIDE, CHONDRUS CRISPUS POWDER (CARRAGEENAN), SODIUM HYALURONATE, POLYSORBATE 60, DIPEPTIDE DIAMINOBUTYROYL BENZYLAMIDE DIACETATE, TRITICUM VULGARE (WHEAT) PROTEIN, BUTYROSPERMUM PARKII (SHEA) BUTTER EXTRACT, SORBITAN ISOSTEARATE, NICOTIANA SYLVESTRIS LEAF CELL CULTURE

PURPOSE

Purpose: Youth aid serum for an immediate and intensive care

WARNINGS

Warnings: For external use only Avoid contact with eyes. Discontinue use if signs of irritation or rashes appear.

KEEP OUT OF REACH OF CHILDREN

INDICATIONS & USAGE

Indications & Usage: Apply morning and night

DOSAGE & ADMINISTRATION

Dosage & Administration: Apply morning and night on clean face and neck prior to ampoule and moisturizer